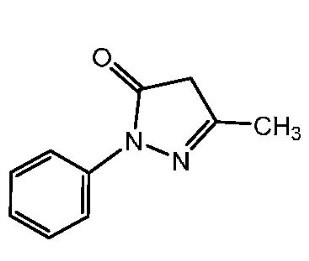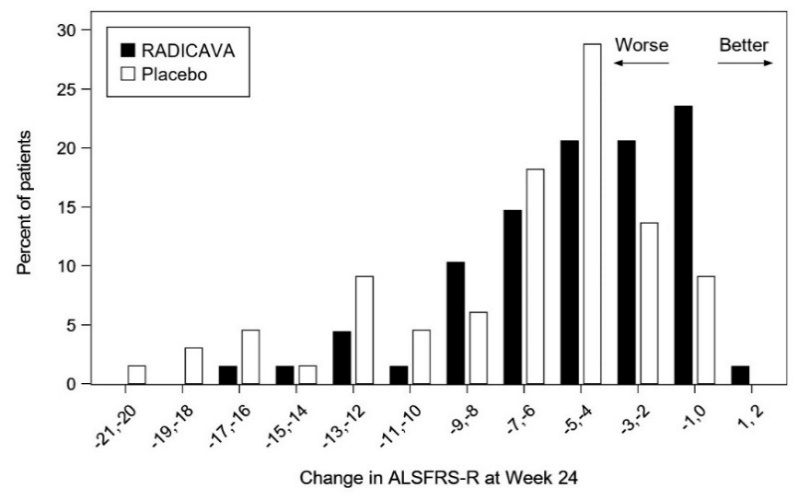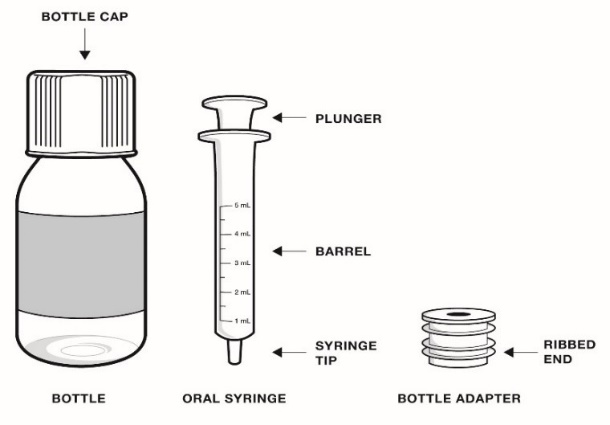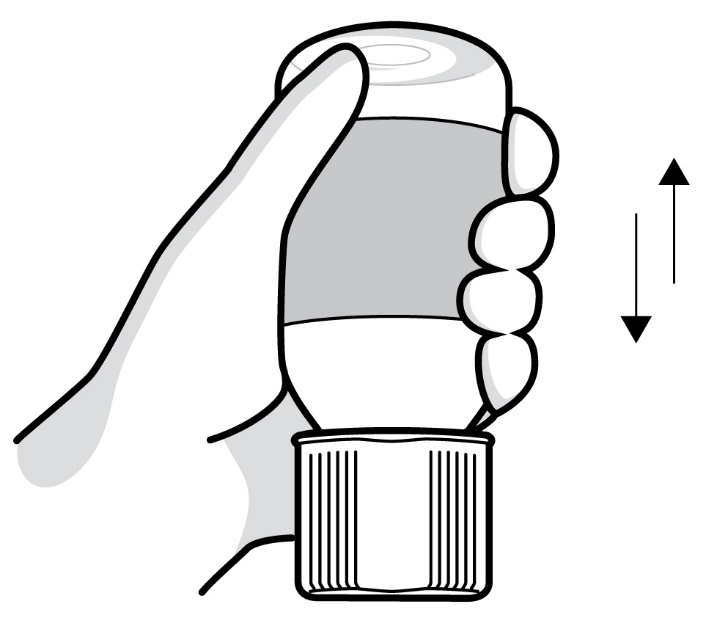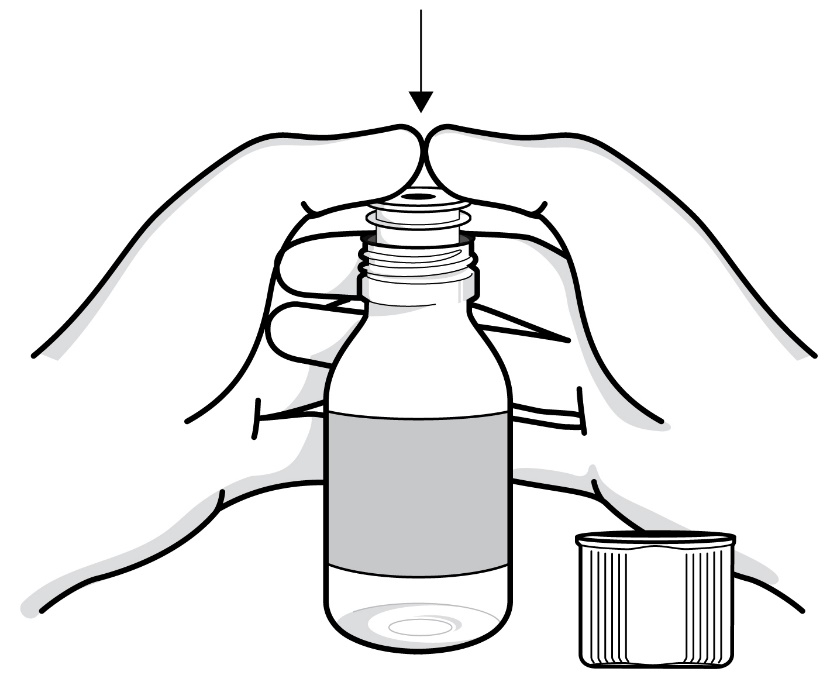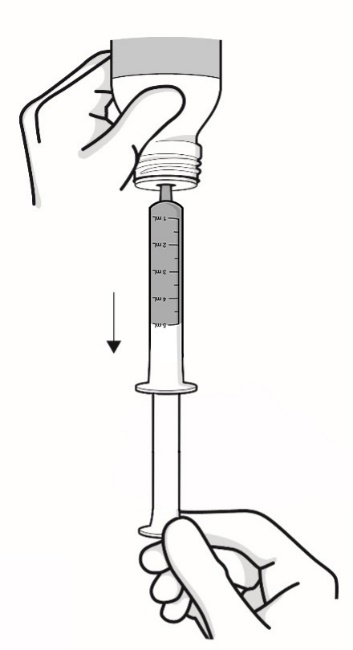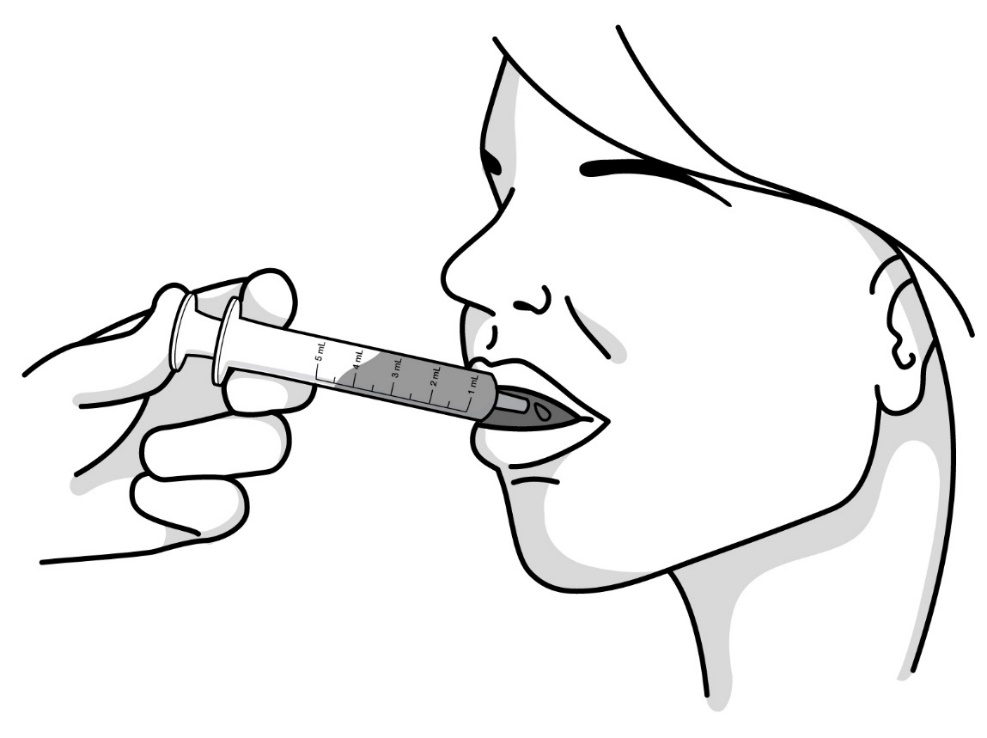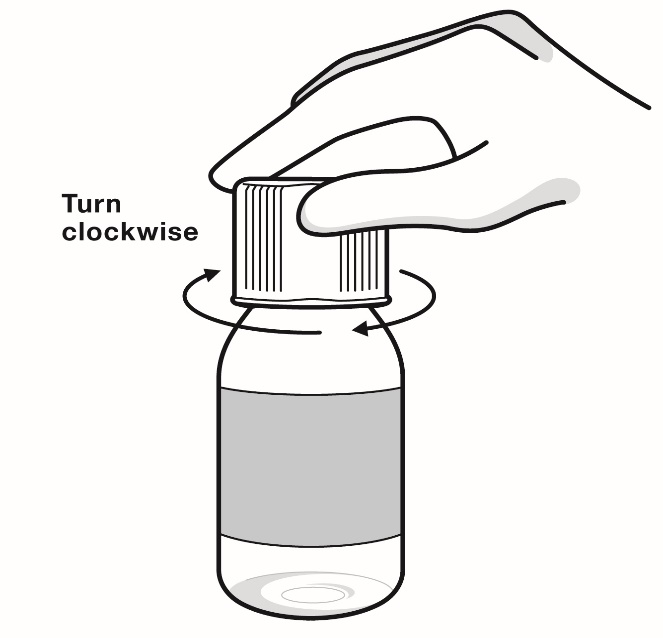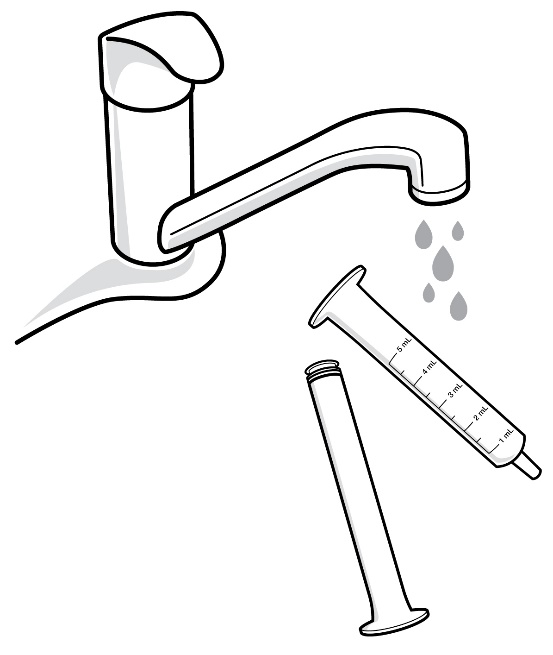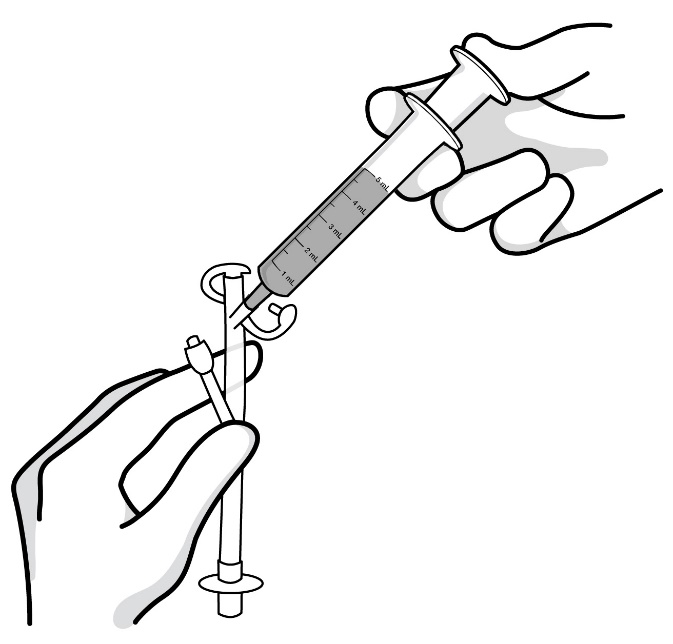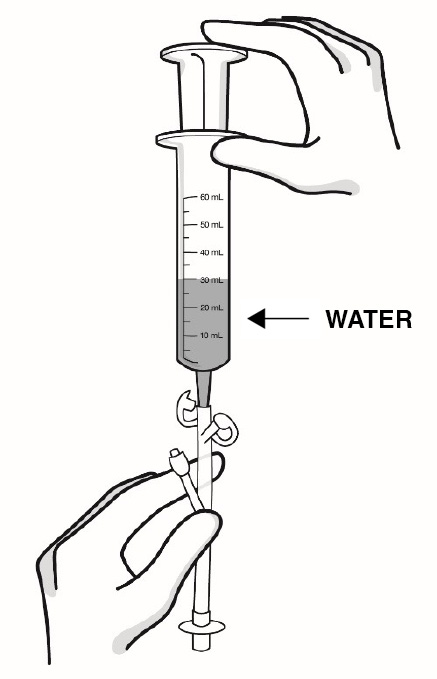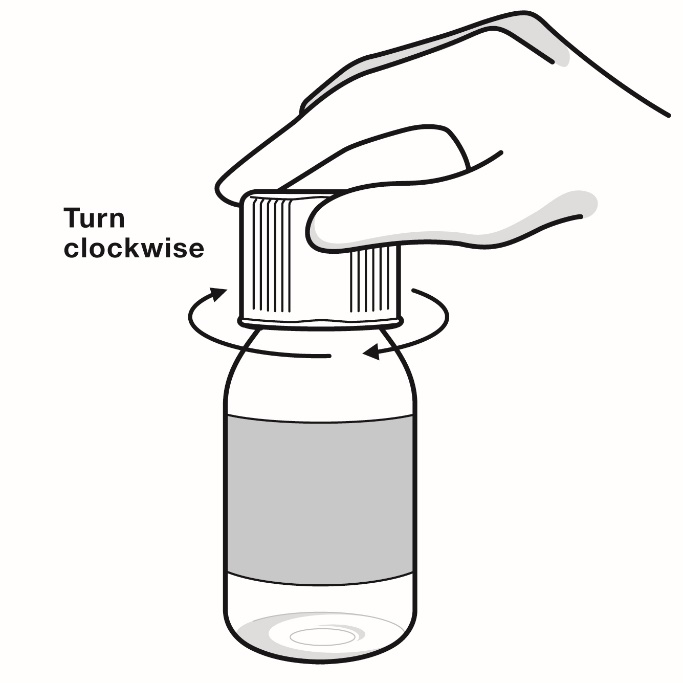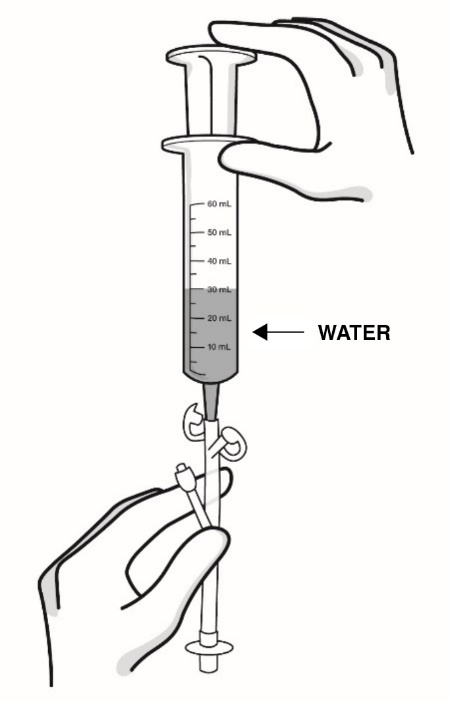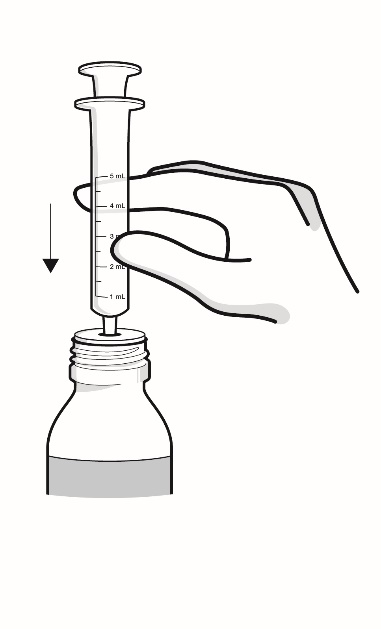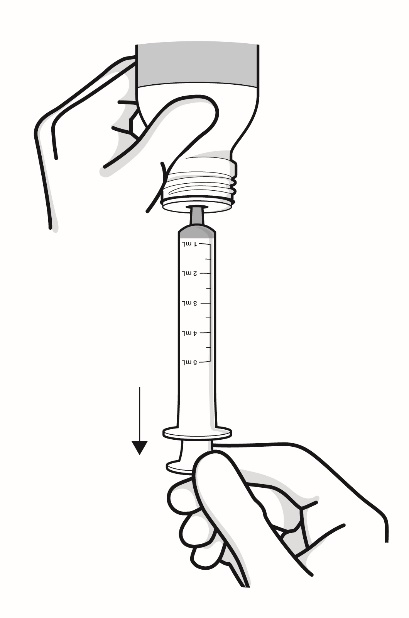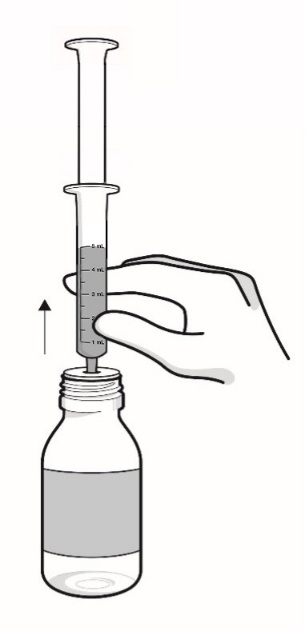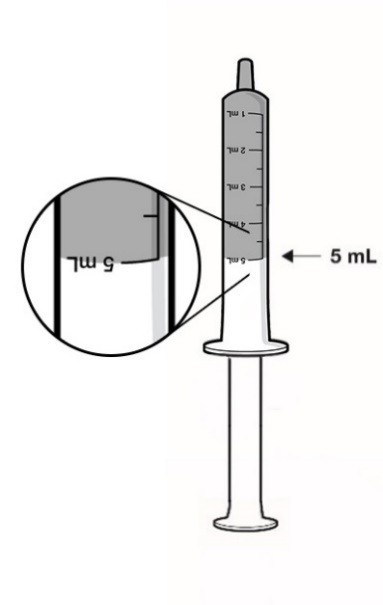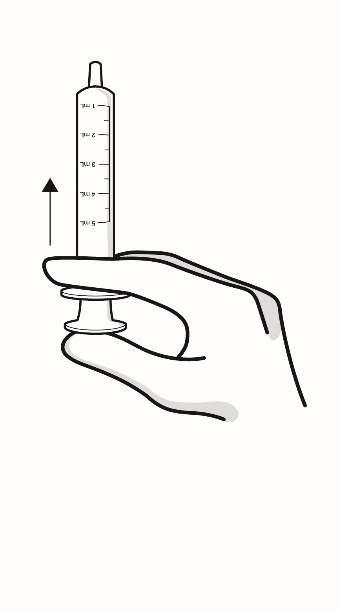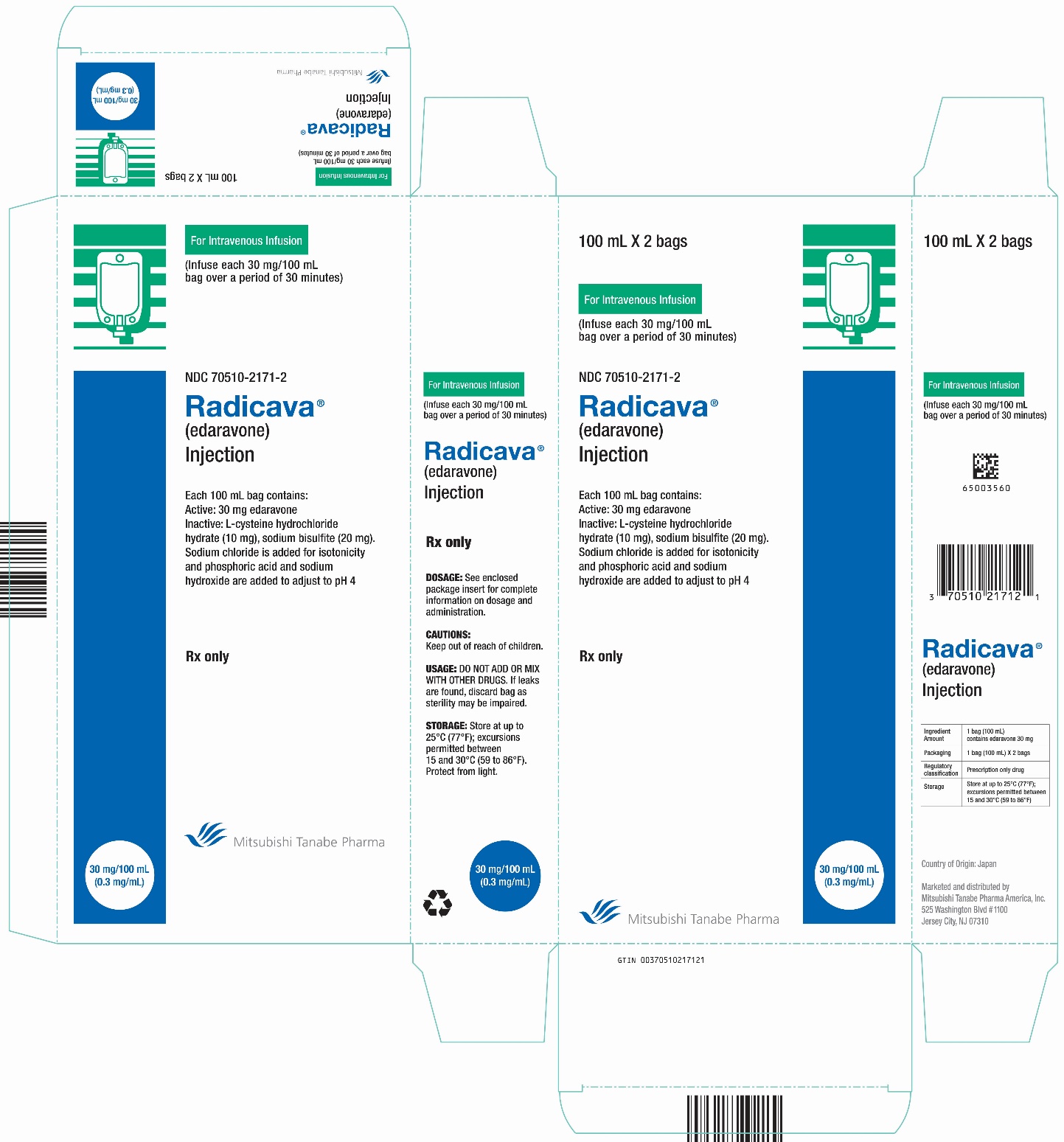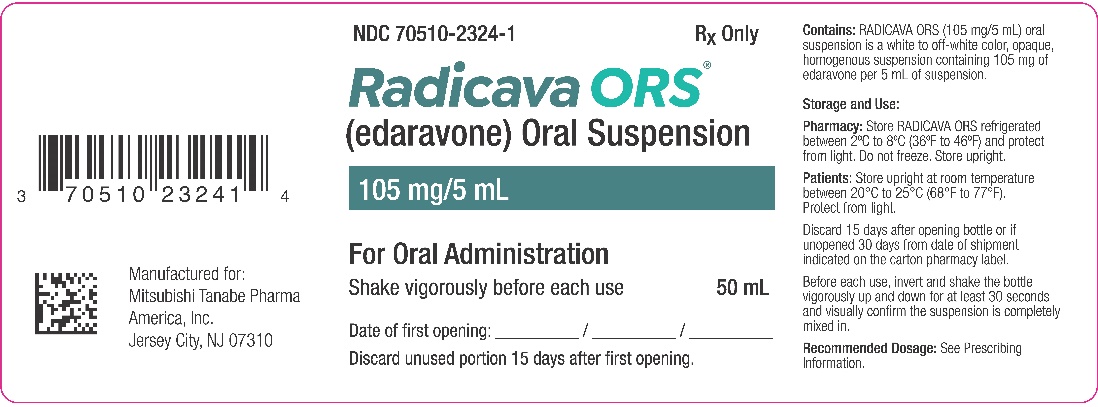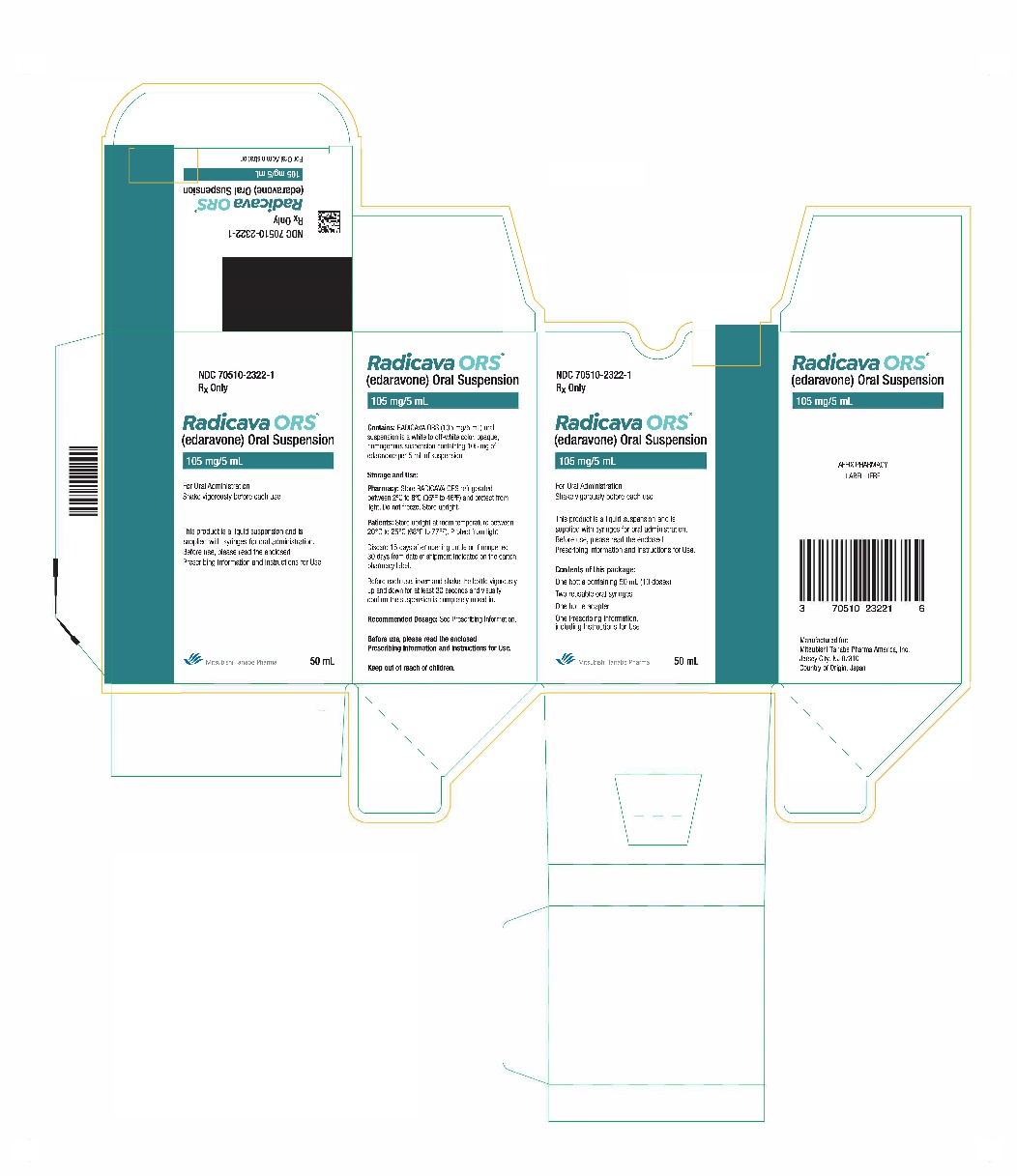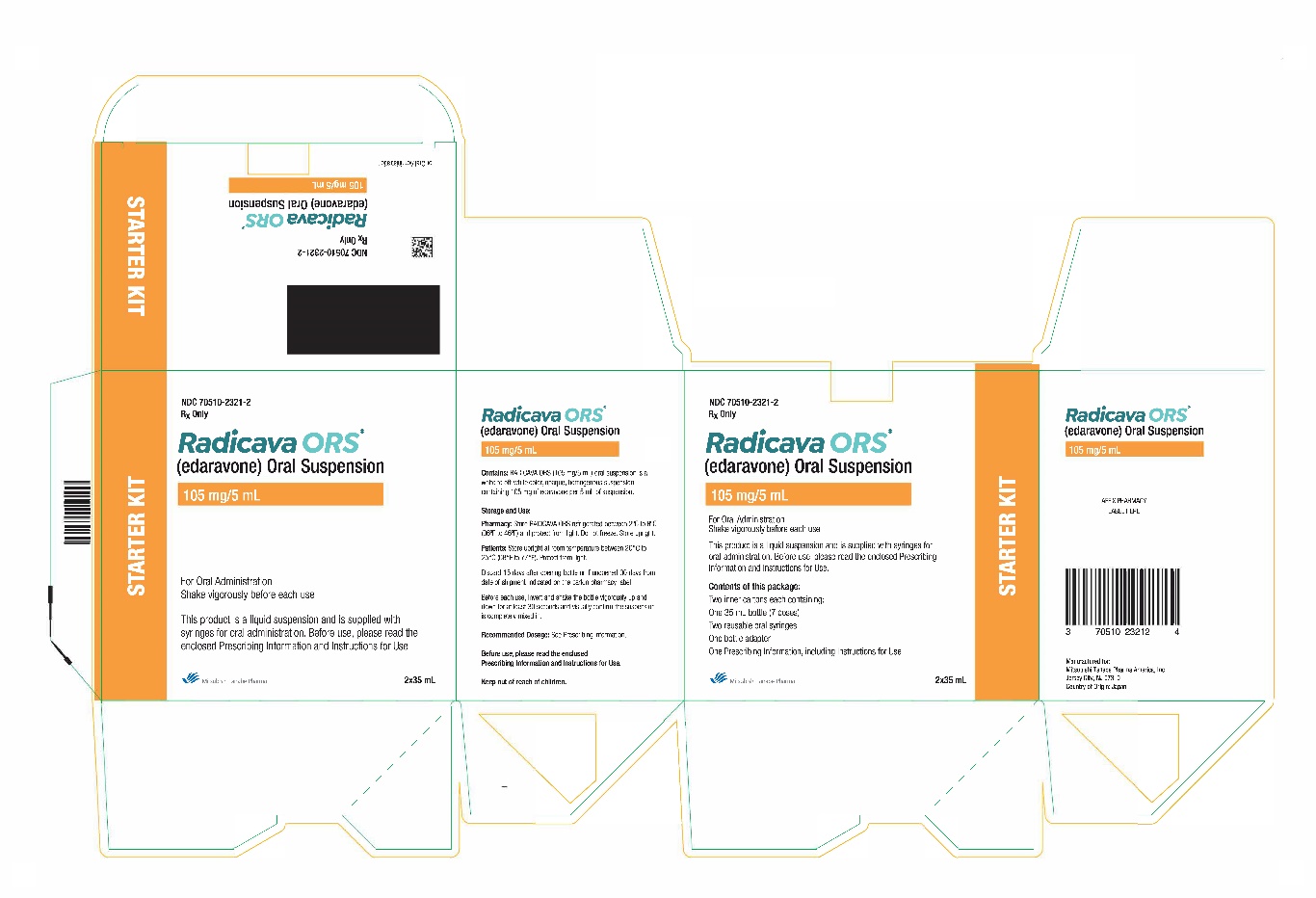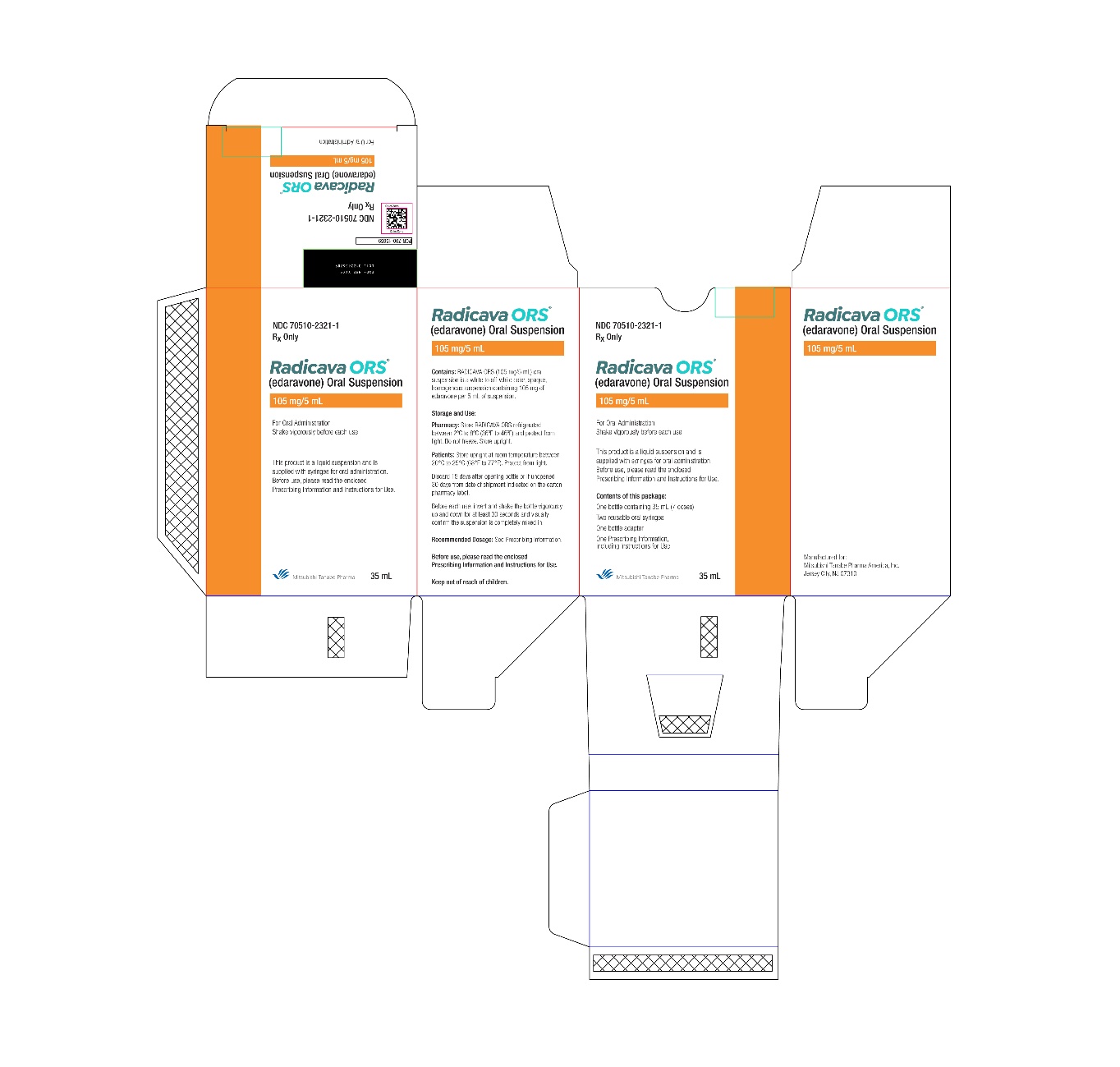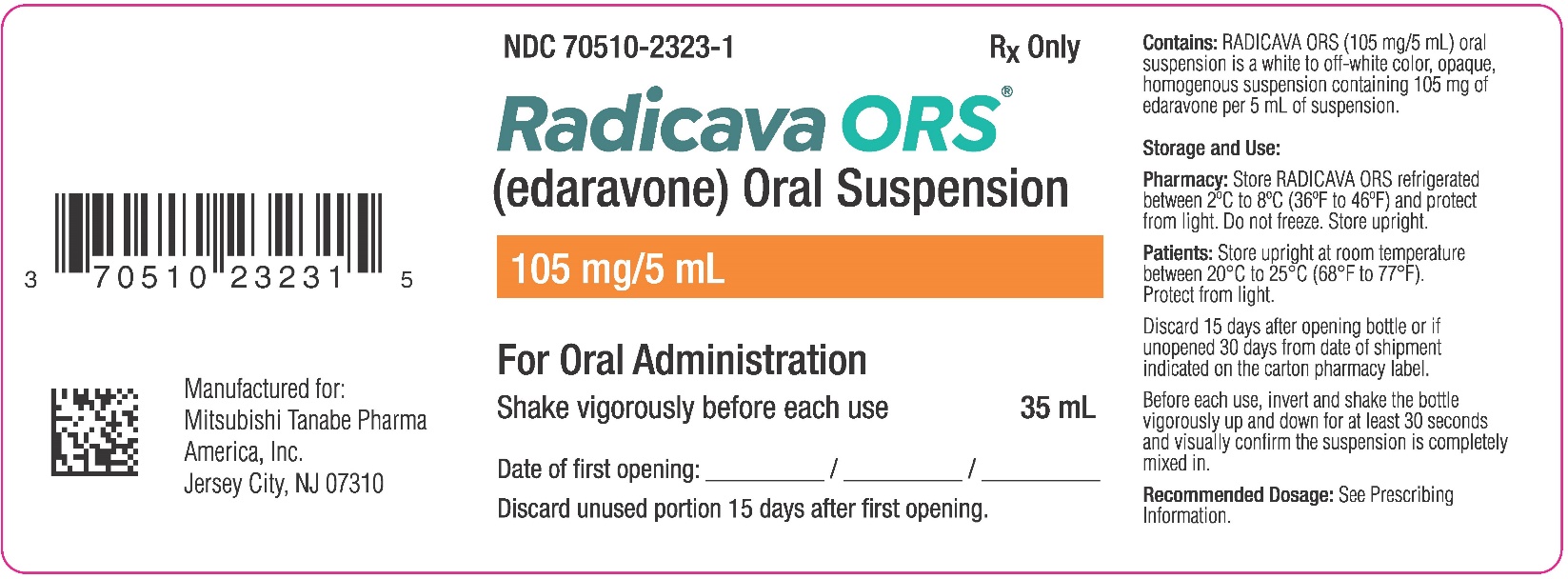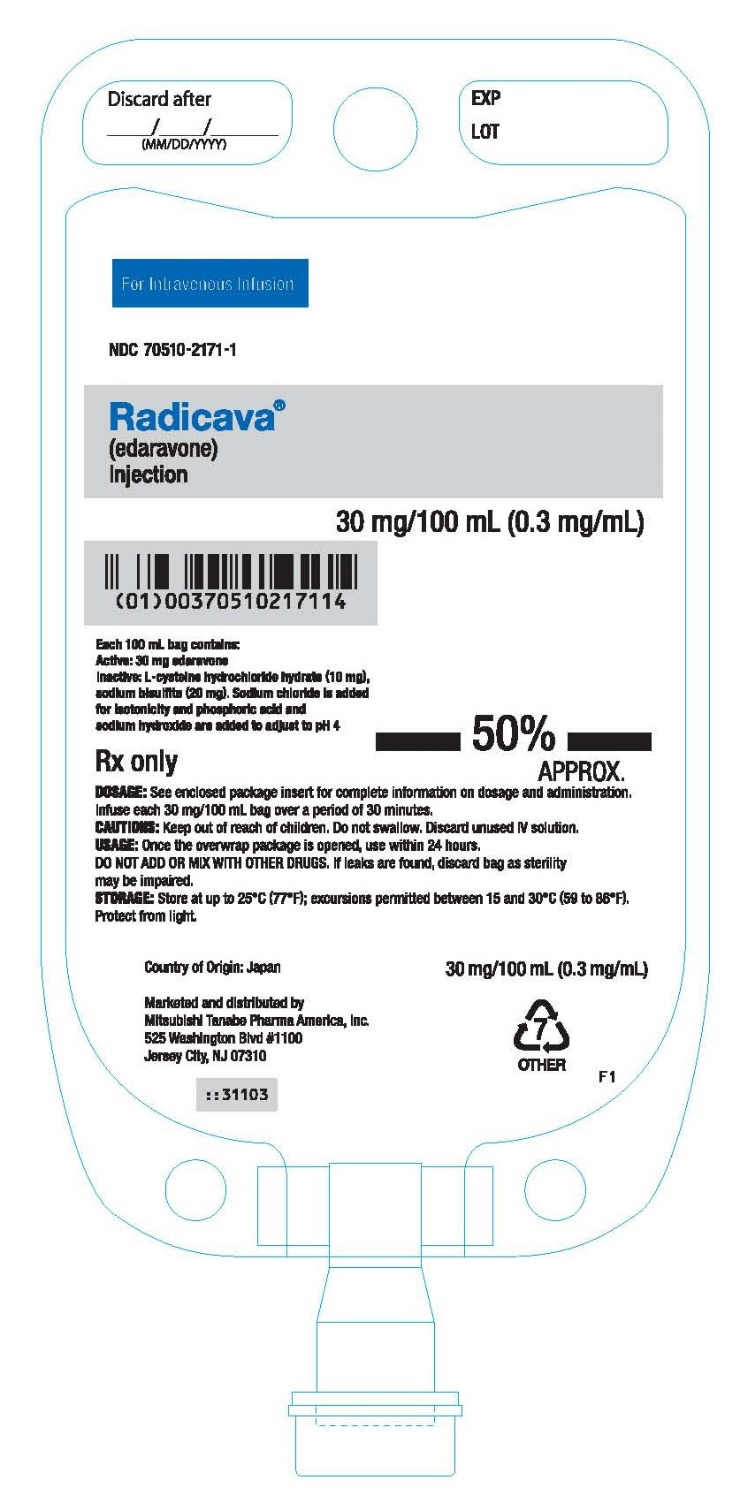 DRUG LABEL: RADICAVA
NDC: 70510-2171 | Form: INJECTION
Manufacturer: Tanabe Pharma America, Inc.
Category: prescription | Type: HUMAN PRESCRIPTION DRUG LABEL
Date: 20251219

ACTIVE INGREDIENTS: EDARAVONE 30 mg/100 mL
INACTIVE INGREDIENTS: SODIUM BISULFITE 20 mg/100 mL; CYSTEINE HYDROCHLORIDE 10 mg/100 mL; SODIUM CHLORIDE; SODIUM HYDROXIDE; PHOSPHORIC ACID; WATER

HIGHLIGHTS OF PRESCRIBING INFORMATION

These highlights do not include all the information needed to use RADICAVA or RADICAVA ORS safely and effectively. See full prescribing information for RADICAVA or RADICAVA ORS.
RADICAVA® (edaravone) injection, for intravenous use
RADICAVA ORS® (edaravone) oral suspension
Initial U.S. Approval: 2017

1 INDICATIONS AND USAGE

RADICAVA and RADICAVA ORS are indicated for the treatment of amyotrophic lateral sclerosis (ALS). (1)

2 DOSAGE AND ADMINISTRATION

- RADICAVA: The recommended dosage is 60 mg administered as an intravenous infusion over 60 minutes (2.1)
- RADICAVA ORS: The recommended dosage is 105 mg (5 mL) taken orally or via feeding tube in the morning after overnight fasting. Food should not be consumed for 1 hour after administration except water (2.1, 2.3)
- For RADICAVA and RADICAVA ORS:
  - Initial treatment cycle: daily dosing for 14 days followed by a 14- day drug-free period (2.1)
  - Subsequent treatment cycles: daily dosing for 10 days out of 14- day periods, followed by 14-day drug-free periods (2.1)

3 DOSAGE FORMS AND STRENGTHS

- Injection: 30 mg/100 mL in a single-dose polypropylene bag (3)
- Oral suspension: 105 mg/5 mL in a multi-dose amber glass bottle (3)

4 CONTRAINDICATIONS

Patients with a history of hypersensitivity to edaravone or any of the inactive ingredients in RADICAVA and/or RADICAVA ORS (4)

5 WARNINGS AND PRECAUTIONS

- Hypersensitivity Reactions: Advise patients to seek immediate medical care (5.1)
- Sulfite Allergic Reactions: RADICAVA and RADICAVA ORS contain sodium bisulfite, which may cause allergic type reactions, including anaphylactic symptoms and asthmatic episodes in susceptible people (5.2)

6 ADVERSE REACTIONS

Most common adverse reactions (at least 10% of patients treated with RADICAVA and greater than placebo) are contusion, gait disturbance, and headache (6.1)

To report SUSPECTED ADVERSE REACTIONS, contact Tanabe Pharma America, Inc. at 1-888-292-0058 or FDA at 1-800-FDA-1088 or www.fda.gov/medwatch.

8 USE IN SPECIFIC POPULATIONS

Pregnancy: Based on animal data, may cause fetal harm. (8.1)

FULL PRESCRIBING INFORMATION

1 INDICATIONS AND USAGE

RADICAVA and RADICAVA ORS are indicated for the treatment of amyotrophic lateral sclerosis (ALS).

2 DOSAGE AND ADMINISTRATION

2.1 Dosage Information

The recommended dosage of RADICAVA and RADICAVA ORS is as follows:

- RADICAVA: an intravenous infusion of 60 mg administered over a 60-minute period
- RADICAVA ORS: 105 mg (5 mL) taken orally or via feeding tube in the morning after overnight fasting [see Dosage and Administration (2.3)]
Administer RADICAVA or RADICAVA ORS according to the following schedule:
- An initial treatment cycle with daily dosing for 14 days, followed by a 14-day drug-free period
- Subsequent treatment cycles with daily dosing for 10 days out of 14-day periods, followed by 14-day drug-free periods

2.2 Preparation and Administration Information for RADICAVA Injection

RADICAVA is for intravenous infusion only.

Preparation

Do not use if the oxygen indicator has turned blue or purple before opening the package. Once the overwrap package is opened, use within 24 hours [see How Supplied/Storage and Handling (16.1,16.2)].

Parenteral drug products should be inspected visually for particulate matter and discoloration prior to administration, whenever solution and container permit.

Administration

Administer each 60 mg dose of RADICAVA injection as two consecutive 30 mg intravenous infusion bags over a total of 60 minutes (infusion rate approximately 1 mg per minute [3.33 mL per minute]).

Promptly discontinue the infusion upon the first observation of any signs or symptoms consistent with a hypersensitivity reaction [see Warnings and Precautions (5.1, 5.2)].

Other medications should not be injected into the infusion bag or mixed with RADICAVA.

2.3 Preparation and Administration Information for RADICAVA ORS Oral Suspension

See the Instruction for Use for further preparation and administration details.

Preparation

Prior to opening the bottle, turn it upside down (invert) and shake vigorously up and down for at least 30 seconds.

Administration

RADICAVA ORS can be administered by mouth or via feeding tube (see Feeding Tube Administration).

RADICAVA ORS should be taken in the morning on an empty stomach after overnight fasting. Food should not be consumed for 1 hour after administration except water [see Clinical Pharmacology (12.3)]. See Table 1 for specific fasting conditions.

Table 1: RADICAVA ORS Administration Relative to Type of Food Consumption
Type of food/caloric supplement consumed | Fasting time before and after RADICAVA ORS dose administration with regards to meal type
High-fat meal (800-1,000 calories, 50% fat) | 8 hours before administration and one hour after administration
Low-fat meal (400-500 calories, 25% fat) | 4 hours before administration and one hour after administration
Caloric supplement (250 calories, e.g., protein drink) | 2 hours before administration and one hour after administration

Administer RADICAVA ORS using a 5 mL oral syringe that comes with the product. A household teaspoon is not an adequate measuring device.

Dispose of any RADICAVA ORS that is not used within 15 days after opening the bottle or within the 30 days from the date of shipment indicated on the carton pharmacy label, which ever happens first.

Feeding Tube Administration

- Nasogastric (NG) tubes or percutaneous endoscopic gastrostomy (PEG) tubes made of silicone, polyvinyl chloride (PVC), or polyurethane can be used
- Before and after administration, use a catheter-tip syringe to flush the tube with at least 1 ounce (30 mL) of water

2.4 Switching from RADICAVA to RADICAVA ORS

Patients treated with 60 mg of RADICAVA intravenous infusion may be switched to 105 mg (5 mL) RADICAVA ORS using the same dosing frequency. Upon switching to RADICAVA ORS, patients should follow RADICAVA ORS dosing recommendations with regards to food consumption [see Dosage and Administration (2.3)].

3 DOSAGE FORMS AND STRENGTHS

RADICAVA is supplied for intravenous infusion in a single-dose polypropylene bag containing 30 mg of edaravone in 100 mL of clear, colorless aqueous solution.

RADICAVA ORS is supplied as an oral suspension in a multi-dose amber glass bottle 105 mg/5 mL of white to off-white color.

4 CONTRAINDICATIONS

RADICAVA and RADICAVA ORS are contraindicated in patients with a history of hypersensitivity to edaravone or any of the inactive ingredients in this product. Hypersensitivity reactions and anaphylactic reactions have occurred [see Warnings and Precautions (5.1, 5.2)].

5 WARNINGS AND PRECAUTIONS

5.1 Hypersensitivity Reactions

Hypersensitivity reactions (redness, wheals, and erythema multiforme) and cases of anaphylaxis (urticaria, decreased blood pressure, and dyspnea) have been reported in spontaneous postmarketing reports with RADICAVA.

Patients should be monitored carefully for hypersensitivity reactions. If hypersensitivity reactions occur, discontinue RADICAVA and/or RADICAVA ORS, treat per standard of care, and monitor until the condition resolves [see Contraindications (4)].

5.2 Sulfite Allergic Reactions

RADICAVA and RADICAVA ORS contain sodium bisulfite, a sulfite that may cause allergic type reactions, including anaphylactic symptoms and life-threatening or less severe asthmatic episodes in susceptible people. The overall prevalence of sulfite sensitivity in the general population is unknown. Sulfite sensitivity occurs more frequently in asthmatic than non-asthmatic people.

6 ADVERSE REACTIONS

The following serious adverse reactions are described elsewhere in the labeling:

- Hypersensitivity Reactions [see Warnings and Precautions (5.1)]
- Sulfite Allergic Reactions [see Warnings and Precautions (5.2)]

6.1 Clinical Trials Experience

Because clinical trials are conducted under widely varying conditions, adverse reaction rates observed in the clinical trials of a drug cannot be directly compared to rates in the clinical trials of another drug and may not reflect the rates observed in practice.

In randomized, placebo-controlled trials, 184 patients with ALS were administered RADICAVA 60 mg in treatment cycles for 6 months. The population consisted of Japanese patients who had a median age of 60 years (range 29-75) and were 59% male. Most (93%) of these patients were living independently at the time of screening.

Most Common Adverse Reactions Observed During Clinical Studies

Table 2 lists the adverse reactions that occurred in ≥ 2% of patients in the RADICAVA-treated group and that occurred at least 2% more frequently than in the placebo-treated group in randomized placebo-controlled ALS trials. The most common adverse reactions that occurred in ≥10% of RADICAVA-treated patients were contusion, gait disturbance, and headache.

Table 2: Adverse Reactions from Pooled Placebo-Controlled Trialsa that Occurred in ≥2% of RADICAVA -Treated Patients and ≥2% More Frequently than in Placebo Patients

Adverse Reaction | RADICAVA IV; (N=184); % | Placebo; (N=184); %
Contusion | 15 | 9
Gait disturbance | 13 | 9
Headache | 10 | 6
Dermatitis | 8 | 5
Eczema | 7 | 4
Respiratory failure, respiratory disorder, hypoxia | 6 | 4
Glycosuria | 4 | 2
Tinea infection | 4 | 2

a Pooled placebo-controlled studies include two additional studies with 231 additional patients, all using the same treatment regimen [see Clinical Studies (14)].

Additional Adverse Reactions with RADICAVA ORS

In an open-label study in patients with ALS (n=185) treated with RADICAVA ORS for 6 months, fatigue was observed in 7.6% of patients.

6.2 Postmarketing Experience

The following adverse reactions have been identified during postapproval use of RADICAVA. Because these reactions are reported voluntarily from a population of uncertain size, it is not always possible to reliably estimate their frequency or establish a causal relationship to drug exposure.

Skin and subcutaneous tissue disorders: Hypersensitivity reactions and anaphylaxis [see Warnings and Precautions (5.1, 5.2)].

8 USE IN SPECIFIC POPULATIONS

8.1 Pregnancy

Risk Summary

There are no adequate data on the developmental risk associated with the use of RADICAVA or RADICAVA ORS in pregnant women. In animal studies, administration of edaravone to pregnant rats and rabbits resulted in adverse developmental effects (increased mortality, decreased growth, delayed sexual development, and altered behavior) at clinically relevant doses. Most of these effects occurred at doses that were also associated with maternal toxicity (see Animal Data).

In the U.S. general population, the estimated background risk of major birth defects and miscarriage in clinically recognized pregnancies is 2-4% and 15-20%, respectively. The background risk for major birth defects and miscarriage in patients with ALS is unknown.

Data

Animal Data

In rats, intravenous administration of edaravone (0, 3, 30, or 300 mg/kg/day) throughout the period of organogenesis resulted in reduced fetal weight at all doses. In dams allowed to deliver naturally, offspring weight was reduced at the highest dose tested. Maternal toxicity was also observed at the highest dose tested. There were no adverse effects on reproductive function in the offspring. A no-effect dose for embryofetal developmental toxicity was not identified; the low dose is less than the recommended human dose of 60 mg for RADICAVA on a body surface area (mg/m^2) basis.

In rabbits, intravenous administration of edaravone (0, 3, 20, or 100 mg/kg/day) throughout the period of organogenesis resulted in embryofetal death at the highest dose tested, which was associated with maternal toxicity. The higher no-effect dose for embryofetal developmental toxicity is approximately 6 times the recommended human dose (RHD) for RADICAVA on a body surface area (mg/m^2) basis.

The effects on offspring of edaravone (0, 3, 20, or 200 mg/kg/day), administered by intravenous injection to rats from GD 17 throughout lactation, were assessed in two studies. In the first study, offspring mortality was observed at the high dose and increased activity was observed at the mid and high doses. In the second study, there was an increase in stillbirths, offspring mortality, and delayed physical development (vaginal opening) at the highest dose tested. Reproduction function in offspring was not affected in either study. Maternal toxicity was evident in both studies at all but the lowest dose tested. The no-effect dose for developmental toxicity (3 mg/kg/day) is less than the RHD on a mg/m^2 basis.

Reproductive and developmental toxicology studies of edaravone using the oral route have not been conducted.

8.2 Lactation

Risk Summary

There are no data on the presence of edaravone in human milk, the effects on the breastfed infant, or the effects of the drug on milk production. Edaravone and its metabolites are excreted in the milk of lactating rats. The developmental and health benefits of breastfeeding should be considered along with the mother’s clinical need for RADICAVA and RADICAVA ORS and any potential adverse effects on the breastfed infant from RADICAVA and RADICAVA ORS or from the underlying maternal condition.

8.4 Pediatric Use

Safety and effectiveness of RADICAVA or RADICAVA ORS in pediatric patients have not been established

8.5 Geriatric Use

Of the 184 patients with ALS who received RADICAVA in 3 placebo-controlled clinical trials, a total of 53 patients were 65 years of age and older, including 2 patients 75 years of age and older. No overall differences in safety or effectiveness were observed between these patients and younger patients, but greater sensitivity of some older individuals cannot be ruled out.

11 DESCRIPTION

The active ingredient in RADICAVA and RADICAVA ORS is edaravone, which is a member of the substituted 2-pyrazolin-5-one class. The chemical name of edaravone is [3-methyl-1-phenyl-2-pyrazolin-5-one]. The molecular formula is C10H10N2O and the molecular weight is 174.20.

The chemical structure is:

Edaravone is a white crystalline powder with a melting point of 129.7°C. It is freely soluble in acetic acid, methanol, or ethanol and slightly soluble in water or diethyl ether.

RADICAVA injection is a clear, colorless liquid provided as a sterile solution.

RADICAVA injection is supplied for intravenous infusion in a polypropylene bag containing 30 mg edaravone in 100 mL isotonic, sterile, aqueous solution, which is further overwrapped with polyvinyl alcohol (PVA) secondary packaging. The overwrapped package also contains an oxygen absorber and oxygen indicator to minimize oxidation. Each bag contains the following inactive ingredients: L-cysteine hydrochloride hydrate (10 mg), sodium bisulfite (20 mg). Sodium chloride is added for isotonicity and phosphoric acid and sodium hydroxide are added to adjust to pH 4.

RADICAVA ORS (edaravone) oral suspension is a white to off-white color, opaque, homogenous suspension containing 105 mg of edaravone per 5 mL of suspension.

RADICAVA ORS contains the following inactive ingredients: L-cysteine hydrochloride hydrate, polyvinyl alcohol, simethicone emulsion, sodium bisulfite, sorbitol, and xanthan gum. Phosphoric acid and sodium hydroxide are added to adjust to pH 4.

12 CLINICAL PHARMACOLOGY

12.1 Mechanism of Action

The mechanism by which RADICAVA and RADICAVA ORS exert their therapeutic effect in patients with ALS is unknown.

12.2 Pharmacodynamics

Cardiac Electrophysiology

At exposures at least 5 times higher than that of the recommended doses of RADICAVA and RADICAVA ORS, edaravone does not prolong the QT interval to any clinically relevant extent.

12.3 Pharmacokinetics

RADICAVA is administered by IV infusion. The maximum plasma concentration (Cmax) of edaravone was reached by the end of infusion. There was a trend of more than dose-proportional increase in area under the concentration-time curve (AUC) and Cmax of edaravone. With multiple-dose administration, edaravone does not accumulate in plasma.

RADICAVA ORS administered orally at the dose of 105 mg, under fasted conditions, was shown to demonstrate an equivalent AUC with RADICAVA (60 mg administered intravenously for 60 min) and Cmax not less than that of RADICAVA. RADICAVA ORS demonstrated similar pharmacokinetics following administration via feeding tubes and oral administration.

In healthy subjects, RADICAVA ORS does not accumulate with once-daily administration, and the maximum plasma concentration (Cmax) and area under the concentration-time curve (AUC) of edaravone is more than dose-proportional over the dose range of 30 to 300 mg (approximately 0.3 and 3 times the recommended dosage, respectively).

Absorption

RADICAVA ORS has a median time to maximum concentration (Tmax) occurring at approximately 0.5 hour (range, 0.25 to 0.75 hours) after fasted oral administration. The absolute oral bioavailability is about 57% because of first pass effect when comparing RADICAVA ORS (105 mg oral suspension) and RADICAVA (60 mg intravenous formulation).

Effect of Food

Following oral administration RADICAVA ORS to healthy subjects 1 hour before or 8 hours after high-fat meals (800-1000 calories, 50% fat), 4 hours after low-fat meals (400-500 calories, 25% fat), or 2 hours after caloric supplement (250 calories, e.g., protein drink), the Cmax and AUC did not decrease significantly (less than 20% and 10% changes in Cmax and AUC, respectively) [see Dosage and Administration (2.3)].

Following oral administration of RADICAVA ORS to healthy subjects, the Cmax decreased by 82%, and the AUC decreased by 61% with a high-fat meal compared to fasted conditions. Following administration of RADICAVA ORS 4 hours after high-fat meals, the Cmax and AUC decreased by 44% and 24%, respectively. Following administration of RADICAVA ORS 2 hours after low-fat meals, the Cmax and AUC decreased by 45% and 21%, respectively.

Distribution

Edaravone is bound to human serum proteins (92%), mainly to albumin, with no concentration dependence in the range of 0.1 to 50 micromol/L. Edaravone has a mean volume of distribution after intravenous administration of 63.1 L.

Elimination

The mean terminal elimination half-life of edaravone is approximately 4.5 to 9 hours. The half-lives of its metabolites are 3 to 6 hours. Following intravenous administration, the total clearance of edaravone is estimated to be 35.9 L/h.

Metabolism

Edaravone is metabolized to a sulfate conjugate and a glucuronide conjugate, which are not pharmacologically active. The glucuronide conjugation of edaravone involves multiple uridine diphosphate glucuronosyltransferase (UGT) isoforms (UGT1A1, UGT1A6, UGT1A7, UGT1A8, UGT1A9, UGT1A10, UGT2B7, and UGT2B17). In human plasma, edaravone is mainly detected as the sulfate conjugate, which is presumed to be formed by sulfotransferases. RADICAVA ORS results in 1.3- and 1.7-fold higher exposures for both sulfate and glucuronide metabolites, respectively, when compared to RADICAVA because of first pass metabolism.

Excretion

In Japanese and Caucasian healthy volunteer studies, edaravone was excreted mainly in the urine as its glucuronide conjugate (60-80% of the dose up to 48 hours). Approximately 6-8% of the dose was recovered in the urine as the sulfate conjugate, and < 1% of the dose was recovered in the urine as the unchanged drug. In vitro studies suggest that the sulfate conjugate of edaravone is hydrolyzed back to edaravone, which is then converted to the glucuronide conjugate in the kidney before excretion into the urine.

Specific Populations

Geriatric Patients

No age effect on edaravone pharmacokinetics has been found [see Use in Specific Populations (8.5)].

Patients with Renal Impairment

Following single IV infusion of 30 mg edaravone (half the recommended dosage of RADICAVA) over 60 minutes, mean Cmax and AUC0-∞ of unchanged edaravone were 1.15- and 1.20-fold greater in the subjects with mild renal impairment (eGFR 60-89 mL/min/1.73m^2), and were 1.25- and 1.29-fold greater in the subjects with moderate renal impairment (eGFR 30-59 mL/min/1.73m^2) when compared to subjects with normal renal function, respectively. These changes in exposures are not considered to be clinically significant and therefore no dosage adjustments are necessary in patients with mild to moderate renal impairment. The effects of severe renal impairment on the pharmacokinetics of edaravone have not been studied.

Patients with Hepatic Impairment

Following single IV infusion of 30 mg edaravone (half of the recommended dose of RADICAVA) over 60 minutes, mean Cmax and AUC0-∞ of unchanged edaravone were 1.20- and 1.07-fold greater in the subjects with mild hepatic impairment (Child-Pugh score 5 or 6), were 1.24- and 1.14-fold greater in the subjects with moderate hepatic impairment (Child-Pugh score 7 to 9), and were 1.20- and 1.19-fold greater in the subjects with severe hepatic impairment (Child-Pugh score 10 to 14) when compared to subjects with normal hepatic function, respectively. These changes in exposures are not considered to be clinically significant and therefore no dosage adjustments are necessary in patients with hepatic impairment.

Male and Female Patients

No gender effect on edaravone pharmacokinetics has been found.

Racial or Ethnic Groups

There were no significant racial differences in Cmax and AUC of edaravone between Japanese and Caucasian subjects.

Drug Interaction Studies

The pharmacokinetics of edaravone is not expected to be significantly affected by inhibitors of cytochrome P450 (CYP) enzymes, UGTs or major transporters. Concomitant oral administration of edaravone 120 mg (higher than the recommended dose of 105 mg for ORS) with sildenafil (CYP3A4 substrate), rosuvastatin (BCRP substrate), and furosemide (OAT3 substrate) did not produce any changes in Cmax and AUC of these drugs.

In vitro studies demonstrated that, at the recommended dosage, edaravone and its metabolites are not expected to significantly inhibit CYP enzymes (CYP1A2, CYP2B6, CYP2C8, CYP2C9, CYP2C19, CYP2D6, and CYP3A), conjugating enzymes UGT1A1 and UGT2B7, or other transporters (P-gp, OATP1B1, OATP1B3, OAT1, OCT2, MATE1, and MATE2-K) in humans. Edaravone and its metabolites are not expected to induce CYP1A2, or CYP2B6, at the recommended dosage of edaravone.

In vitro data indicated that edaravone was not a substrate of OATP1B1 or OATP1B3.

13 NONCLINICAL TOXICOLOGY

13.1 Carcinogenesis, Mutagenesis, Impairment of Fertility

Carcinogenesis

In a 26-week carcinogenicity study in male and female transgenic (Tg rasH2) mice, oral administration of edaravone (0 [water control], 0 [vehicle control], 100, 150, or 350 mg/kg) resulted in no increase in tumors.

In a 2-year carcinogenicity study in rats, oral administration of edaravone (0, 50, 100, or 200 mg/kg in males; 0, 50, 100, or 250 mg/kg in females) resulted in no increase in tumors.

Carcinogenicity studies of edaravone using the intravenous route have not been conducted.

Mutagenesis

Edaravone was negative in in vitro (bacterial reverse mutation and Chinese hamster lung chromosomal aberration) and in vivo (mouse micronucleus) assays.

Impairment of Fertility

Intravenous administration of edaravone (0, 3, 20, or 200 mg/kg) prior to and throughout mating in male and female rats and continuing in females to gestation day 7 had no effect on fertility; however, disruption of the estrus cycle and mating behavior was observed at the highest dose tested. No effects on reproductive function were observed at the lower doses, which are up to approximately 3 times the RHD for RADICAVA (60 mg) on a body surface area (mg/m^2) basis.

Fertility studies of edaravone using the oral route have not been conducted.

13.2 Animal Toxicology and/or Pharmacology

Oral administration of edaravone (0, 10, 30, 100, or 300 mg/kg/day) in dogs for 39 weeks resulted in neurotoxicity, characterized by white matter vacuolation in the spinal cord and vacuolation and nerve fiber atrophy in the sciatic nerve, at the two highest doses tested. The microscopic findings were accompanied by gait abnormalities, loss of patellar reflex, and inability to rise. Plasma edaravone exposures (Cmax and AUC) at the higher no-effect dose for neurotoxicity (30 mg/kg/day) were approximately 2 times those in humans at the recommended human dose of RADICAVA ORS (105 mg).

14 CLINICAL STUDIES

The efficacy of RADICAVA ORS is based on a bioavailability study comparing RADICAVA and RADICAVA ORS [see Clinical Pharmacology (12.3)].

The efficacy of RADICAVA for the treatment of ALS was established in a 6-month, randomized, placebo- controlled, double-blind study conducted in Japanese patients with ALS who were living independently and met the following criteria at screening:

1. Functionality retained most activities of daily living (defined as scores of 2 points or better on each individual item of the ALS Functional Rating Scale – Revised [ALSFRS-R; described below])
2. Normal respiratory function (defined as percent-predicted forced vital capacity values of [%FVC] ≥80%)
3. Definite or Probable ALS based on El Escorial revised criteria
4. Disease duration of 2 years or less

The study enrolled 69 patients in the RADICAVA arm and 68 in the placebo arm. Baseline characteristics were similar between these groups, with over 90% of patients in each group being treated with riluzole.

RADICAVA was administered as an intravenous infusion of 60 mg given over a 60-minute period according to the following schedule:

  - An initial treatment cycle with daily dosing for 14 days, followed by a 14-day drug-free period (Cycle 1)
  - Subsequent treatment cycles with daily dosing for 10 days out of 14-day periods, followed by 14-day drug-free periods (Cycles 2-6).

The primary efficacy endpoint was a comparison of the change between treatment arms in the ALSFRS-R total scores from baseline to Week 24. The ALSFRS-R scale consists of 12 questions that evaluate the fine motor, gross motor, bulbar, and respiratory function of patients with ALS (speech, salivation, swallowing, handwriting, cutting food, dressing/hygiene, turning in bed, walking, climbing stairs, dyspnea, orthopnea, and respiratory insufficiency). Each item is scored from 0-4, with higher scores representing greater functional ability. The decline in ALSFRS-R scores from baseline was significantly less in the RADICAVA-treated patients as compared to placebo (see Table 3). The distribution of change in ALSFRS-R scores from baseline to Week 24 by percent of patients is shown in Figure 1.

Table 3: Analysis of Change from Baseline to Week 24 in ALSFRS-R Scores

Treatment | Change from Baseline; LS Mean ± SE (95% CI) | Treatment Difference (RADICAVA – placebo [95% CI]) | p-value
RADICAVA IV | −5.01±0.64 | 2.49 (0.99, 3.98) | 0.0013
Placebo | −7.50±0.66

Figure 1 Distribution of Change from Baseline to Week 24 in ALSFRS-R Scores

16 HOW SUPPLIED/STORAGE AND HANDLING

16.1 How Supplied

RADICAVA

RADICAVA is supplied as a 30 mg/100 mL (0.3 mg/mL) clear, colorless, sterile solution for intravenous infusion in single-dose polypropylene bags, each overwrapped with polyvinyl alcohol (PVA) secondary packaging containing an oxygen absorber and oxygen indicator, which should be pink to reflect appropriate oxygen levels [see Dosage and Administration (2.2) and How Supplied/Storage and Handling (16.2)]. These are supplied in cartons as listed below.

NDC 70510-2171-1 30 mg/100 mL (0.3 mg/mL) single-dose bag

NDC 70510-2171-2 2 bags per carton

RADICAVA ORS

RADICAVA ORS is supplied in a white to off-white suspension in multi-dose child resistant 60 mL amber glass bottle which is supplied as two configurations:

- RADICAVA ORS Starter Kit (14-day treatment cycle), including two (2) inner cartons, each containing one (1) bottle of 735 mg/35mL (105 mg/5 mL dose), two oral dosing syringes and one bottle adapter.
- RADICAVA ORS Kit (10-day treatment cycle), including one (1) bottle of 1050 mg/50 mL (105 mg/5 mL dose) with two oral dosing syringes and one bottle adapter.

These are supplied in cartons as listed below:

Unit of sale | NDC number | Package configuration
RADICAVA ORS Starter Kit | NDC 70510-2321-1 | Carton of One (1) bottle of 35mL (105 mg/5 mL dose)
RADICAVA ORS Starter Kit | NDC 70510-2321-2 | Carton of two (2) NDC 70510-2321-1
RADICAVA ORS Kit | NDC 70510-2322-1 | Carton of One (1) bottle of 50 mL (105 mg/5 mL dose)

16.2 Storage and Handling

RADICAVA

Store RADICAVA at up to 25°C (77°F). Excursions permitted from 15°C to 30°C (59°F to 86°F) [see USP Controlled Room Temperature]. Protect from light. Store in overwrapped package to protect from oxygen degradation until time of use. The oxygen indicator will turn blue or purple if the oxygen has exceeded acceptable levels. Once the overwrap package is opened, use within 24 hours.

RADICAVA ORS

Pharmacy

Store RADICAVA ORS refrigerated between 2ºC to 8ºC (36°F to 46°F) and protect from light. Do not freeze. Store upright.

Patient

Store RADICAVA ORS upright at room temperature between 20°C to 25°C (68°F to 77°F). Protect from light.

Discard 15 days after opening bottle or if unopened 30 days from date of shipment indicated on the carton pharmacy label.

17 PATIENT COUNSELING INFORMATION

Advise the patients to read the FDA-approved patient labeling (Patient Information and Instructions for Use).

Hypersensitivity Reactions

Advise patients to seek immediate medical care if they experience signs or symptoms of a hypersensitivity reaction [see Warnings and Precautions (5.1)].

Sulfite Allergic Reactions

Advise patients about potential for sulfite sensitivity. Inform patients that RADICAVA and RADICAVA ORS contain sodium bisulfite, which may cause allergic type reactions including anaphylactic symptoms and life-threatening or less severe asthmatic episodes, and to seek immediate medical care if they experience these signs or symptoms [see Warnings and Precautions (5.2)].

Pregnancy and Breastfeeding

Advise patients to notify their healthcare provider if they become pregnant or intend to become pregnant during RADICAVA or RADICAVA ORS therapy [see Use in Specific Populations (8.1)].

Advise patients to notify their healthcare provider if they intend to breastfeed or are breastfeeding an infant [see Use in Specific Populations (8.2)].

RADICAVA ORS Administration

Advise patients to take RADICAVA ORS in the morning on an empty stomach. Instruct patients to fast 8 hours before each dose if they consume a high-fat meal, 4 hours before each dose if they consume a low-fat meal, or 2 hours before each dose if they consume a caloric supplement [see Dosage and Administration (2.3) and Clinical Pharmacology (12.3)]. Also instruct patients to not to consume food for 1 hour after each dose.

Advise caregivers, if administering RADICAVA ORS via feeding tube, to use a catheter-tip syringe and flush the feeding tube with approximately 1 ounce (30 mL) of water before and after use (see Instructions for Use).

Marketed and distributed by:

Tanabe Pharma America, Inc.

Jersey City, NJ 07310

RADICAVA and RADICAVA ORS are registered trademarks of K.K. BCJ-94.

© 2025 Tanabe Pharma America, Inc. All rights reserved.

22022-3 Iss. 12/2025

Information for Patients

PATIENT INFORMATION

RADICAVA (ra di ká vah)

(edaravone injection)

for intravenous infusion

RADICAVA ORS (ra di ká vah o r s)

(edaravone oral suspension)

administered by mouth or via feeding tube

What are RADICAVA® and RADICAVA ORS®?

RADICAVA and RADICAVA ORS are prescription medicines used to treat people with amyotrophic lateral sclerosis (ALS).

It is not known if RADICAVA or RADICAVA ORS are safe and effective in children.

Do not receive RADICAVA or RADICAVA ORS if you are allergic to edaravone or any of the ingredients in RADICAVA and RADICAVA ORS. See the end of this leaflet for a complete list of ingredients in RADICAVA and RADICAVA ORS.

Before you take RADICAVA or RADICAVA ORS, tell your healthcare provider about all of your medical conditions, including if you:

- have asthma.
- are allergic to other medicines.
- are pregnant or plan to become pregnant. It is not known if RADICAVA or RADICAVA ORS will harm your unborn baby.
- are breastfeeding or plan to breastfeed. It is not known if RADICAVA or RADICAVA ORS passes into your breastmilk.
You and your healthcare provider should decide if you will receive RADICAVA or RADICAVA ORS or breastfeed.

Tell your healthcare provider about all the medicines you take, including prescription and over-the-counter medicines, vitamins, and herbal supplements.

How will I receive RADICAVA?

- You will be prescribed RADICAVA by a healthcare provider and told how often you will receive RADICAVA.
- RADICAVA will be given by intravenous (IV) infusion into your vein.
- It takes about 1 hour to receive the full dose of RADICAVA.
- Your healthcare provider will monitor you closely during your treatment with RADICAVA.

How will I take RADICAVA ORS?

- See the detailed Instructions for Use on how to take RADICAVA ORS at the end of this Patient Information leaflet.
- You will be prescribed RADICAVA ORS by a healthcare provider and told how often you will take RADICAVA ORS.
- RADICAVA ORS is to be taken by mouth or by using a feeding tube.
- RADICAVA ORS should be taken in the morning on an empty stomach. You should stop eating at bedtime.
- Do not eat or drink anything 8 hours before each dose of RADICAVA ORS if you eat a high-fat meal.
- Do not eat or drink anything 4 hours before each dose of RADICAVA ORS if you eat a low-fat meal.
- Do not eat or drink anything 2 hours before each dose of RADICAVA ORS if you take a calorie supplement.
- You should wait at least 1 hour after taking your medicine before eating or drinking anything except water.

What are the possible side effects of RADICAVA and RADICAVA ORS?

RADICAVA and RADICAVA ORS may cause serious side effects including:

1. Hypersensitivity (allergic) reactions. Hypersensitivity reactions have happened in people receiving RADICAVA or taking RADICAVA ORS and can happen after your medicine has been given. Tell your healthcare provider right away or go to the nearest emergency room if you have any of the following symptoms:

2. Sulfite allergic reactions. RADICAVA and RADICAVA ORS contain sodium bisulfite, a sulfite that may cause a type of allergic reaction that can be serious and life-threatening. Sodium bisulfite can also cause less severe allergic reactions, for example, asthma episodes, in certain people. Sulfite sensitivity can happen more often in people who have asthma than in people who do not have asthma. Tell your healthcare provider right away or go to the nearest emergency room if you have any of the following symptoms:

Your healthcare provider will monitor you during treatment to watch for signs and symptoms of all the serious side effects and allergic reactions.

The most common side effects of RADICAVA and RADICAVA ORS include bruising (contusion), problems walking (gait disturbance), and headache.

These are not all the possible side effects of RADICAVA and RADICAVA ORS. For more information, ask your healthcare provider or pharmacist.

Call your doctor for medical advice about side effects. You may report side effects to FDA at 1-800-FDA-1088.

You may also report side effects to www.fda.gov/medwatch or Tanabe Pharma America, Inc. at 1-888-292-0058.

What are the ingredients in RADICAVA and RADICAVA ORS?

Active ingredient: edaravone

RADICAVA Inactive ingredients: L-cysteine hydrochloride hydrate, sodium bisulfite, sodium chloride, phosphoric acid, and sodium hydroxide.

RADICAVA ORS Inactive ingredients: L-cysteine hydrochloride hydrate, polyvinyl alcohol, simethicone emulsion, sodium bisulfite, sorbitol, and xanthan gum. Phosphoric acid and sodium hydroxide are added to adjust to pH 4.

Marketed and distributed by:

Tanabe Pharma America, Inc.

Jersey City, NJ 07310

For more information, go to www.Radicava.com or call 1-888-292-0058.

RADICAVA and RADICAVA ORS are registered trademarks of K.K. BCJ-94.

© 2025 Tanabe Pharma America, Inc. All rights reserved.

This Patient Information has been approved by the U.S. Food and Drug Administration 22022-3 Issued: 12/2025

Instructions for Use

RADICAVA (ra di ká vah) ORS

(edaravone)

oral suspension

Read this Instructions for Use before you take RADICAVA ORS® for the first time and each time you get a refill. There may be new information. This information does not take the place of talking to your healthcare provider about your medical condition or treatment.
Important information about measuring RADICAVA ORS: Always measure your prescribed dose of RADICAVA ORS using the oral syringe provided. Ask your healthcare provider or pharmacist who provided the medicine any questions you have about how to measure your prescribed dose. If you miss a dose, do not take 2 doses of RADICAVA ORS the next day. Do not take a dose of RADICAVA ORS on days 15 through 28.
  How to prepare RADICAVA ORS: Keep this Instructions for Use handy when preparing the treatment.
3. If your healthcare provider prescribes a Starter Kit, you will receive 2 bottles of RADICAVA ORS. Each bottle will contain 35 mL of RADICAVA ORS for a total of 70 mL to be used for your first treatment cycle of 14 days. Only open the second bottle when you have finished the first bottle.
4. If you were not prescribed the Starter Kit, for each treatment cycle you will receive 1 bottle of RADICAVA ORS that contains a total of 50 mL of RADICAVA ORS. After the first treatment cycle, RADICAVA ORS is to be used for 10 days out of 14 day periods.
5. Only use the bottle adapter and the 2 reusable 5 mL oral syringes provided with the bottle. Do not use a household teaspoon to measure your medicine.

How to store RADICAVA ORS:

- Store RADICAVA ORS upright at room temperature between 68°F to 77°F (20°C to 25°C). Protect from light.
- Opening the bottle:
  - When you open the bottle of RADICAVA ORS for the first use, write the date you open the bottle on the bottle label.
  - After opening the bottle of RADICAVA ORS, use within 15 days.
- After a bottle of RADICAVA ORS has been opened and used, a white crust may form on the neck or on the side of the bottle. This is due to normal use and RADICAVA ORS can continue to be uses as prescribed.
- Keep bottle tightly closed between each use.
- Throw away (discard) any RADICAVA ORS that is not used within 15 days after opening the bottle or within 30 days from the date of shipment shown on the carton pharmacy label, whichever happens first. Ask your pharmacist how to properly throw away (discard) RADICAVA ORS you are no longer able to use.
- Keep RADICAVA ORS and all medicines out of the reach of children.

Each RADICAVA ORS carton contains:

- 1 RADICAVA ORS bottle
- 1 bottle adapter
- 2 (5 mL) reusable oral syringes

Use a new 5 mL oral syringe and bottle adapter when using a new bottle of RADICAVA ORS (see Figure A)

Figure A

Important information:

- Keep these instructions for future use.
- Do not share RADICAVA ORS with anyone else.
- Call your doctor for medical advice about side effects. You may report side effects to FDA at 1-800-FDA-1088.
- People who have problems using their hands may need assistance to draw up and give the correct dose of RADICAVA ORS.

How to take RADICAVA ORS:

Take RADICAVA ORS as prescribed by your healthcare provider.

Dosing Information:
RADICAVA ORS has 2 different dosing schedules:
3. For the first treatment cycle, you will take RADICAVA ORS every day for 14 days, followed by 14 days without the medicine.
4. For the cycles after the first treatment cycle, you will take RADICAVA ORS daily for 10 out of 14 days, followed by 14 days without the medicine.
How RADICAVA ORS will be provided:
6. If your healthcare provider prescribes the Starter Kit, you will receive 2 bottles of RADICAVA ORS. Each bottle contains 35 mL of RADICAVA ORS for a total of 70 mL to deliver 14 doses.
  - There may be some medicine that remains in each bottle after the dose on day 7 and day 14 of the first treatment cycle. Throw away (discard) any medicine that remains.
7. If you were not prescribed the starter kit, for each treatment cycle, you will receive 1 bottle of RADICAVA ORS that contains a total of 50 mL of RADICAVA ORS to deliver 10 doses.
  - There may be some medicine that remains in each bottle after 10 doses. Throw away (discard) any medicine that remains.
Fasting Information:
9. Do not eat or drink anything 8 hours before each dose of RADICAVA ORS if you eat a high-fat meal.
10. Do not eat or drink anything 4 hours before each dose of RADICAVA ORS if you eat a low-fat meal.
11. Do not eat or drink anything 2 hours before each dose of RADICAVA ORS if you take a calorie supplement.
12. You should wait at least 1 hour after taking your medicine before eating or drinking anything except water.

Step 1: Before each use of RADICAVA ORS: Before opening the bottle, turn it upside down (invert) and shake vigorously up and down for at least 30 seconds (see Figure B). Look at the liquid medicine to make sure it is mixed well. If you see any small pieces at the bottom of the bottle, invert the bottle and shake it up and down for another 30 seconds or until you can no longer see the pieces at the bottom of the bottle (see Figure B). If the liquid medicine all looks the same, you can proceed to Step 2.

Shake up and down for at least 30 seconds

Figure B

Step 2: Open the bottle by firmly pressing down on the bottle cap and turning it counterclockwise (to the left). Place the open bottle upright on a flat surface. Do not throw away the bottle cap; you will need to replace it after taking each dose.

First time use of a bottle only. This must only be done 1 time for each bottle. Insert the ribbed end of the bottle adapter into the bottle by firmly pressing it in as far as it will go (see Figure C). Do not remove the bottle adapter.

Figure C

Step 3: Remove the oral syringe from plastic wrap and make sure the plunger is inserted all the way into the barrel. Push the oral syringe plunger toward its tip to remove excess air (see Figure D). Insert the oral syringe into the opening of the bottle adapter until it is firmly in place (see Figure E). Turn the bottle upside down and slowly pull the plunger to remove a small amount of liquid (see Figure F).

Figure D

Figure E

Figure F

Step 4: Keep the bottle upside down and pull the plunger until it goes up to the last line (5 mL) (see Figure G). While keeping the plunger in the same position, turn the bottle upright, and place it carefully on a flat surface. Remove the oral syringe by gently twisting or pulling it out from the bottle (see Figure H). Check the amount of medicine again before moving on to the next step (see Figure I).

Note: Do not remove the oral syringe while the bottle is upside down (medicine may leak out through the adapter).

Note: If the dose is not correct, insert the oral syringe tip firmly into the bottle adapter. Push the plunger all the way in so that the medicine flows back into the bottle. Turn the bottle upside down. Repeat Step 4.

Figure G

Figure H

Figure I

Step 5: Place the tip of the oral syringe in the mouth and aim towards the inside of the cheek. Slowly press down on the plunger until the oral syringe is empty. Swallow all of the medicine (see Figure J). If needed, you can use up to 8 ounces or 1 cup of water to help swallow the medicine.

Note: It is normal for a small amount of medicine to remain in the tip of the syringe after taking.

Figure J

Step 6: Leave the bottle adapter inside the bottle. Place the bottle cap on the bottle and turn the cap clockwise (to the right). Keep bottle tightly closed between each use (see Figure K).

Figure K

Step 7: Remove the plunger from the oral syringe barrel by pulling the plunger and the barrel away from each other. Rinse the oral syringe (plunger and barrel) with water only. Allow it to air dry.

Figure L

Step 8: When the oral syringe (plunger and barrel) is dry, put the plunger back into the oral syringe barrel. Do not throw away the oral syringe. Store the syringe in a clean, dry place.

You must complete Steps 1 through 4 under "How to take RADICAVA ORS" before starting Step 9 under "How to take a dose of RADICAVA ORS oral suspension through a feeding tube."

How to take a dose of RADICAVA ORS oral suspension through a feeding tube:

Step 9: Using a catheter-tip syringe, flush the feeding tube with 1 ounce (30 mL) of water (see Figure M).

Figure M

Step 10: Place the oral syringe provided (containing the 5 mL of RADICAVA ORS) into the feeding tube. Slowly push down the plunger until the oral syringe is empty (see Figure N).

Figure N

Step 11: Using a catheter-tip syringe, flush the feeding tube with 1 ounce (30 mL) of water after taking dose of RADICAVA ORS (see Figure O).

Figure O

Step 12: Leave the adapter in the bottle. Place the bottle cap on the bottle and turn it clockwise (to the right) to close the bottle. Keep the bottle tightly closed between each use (see Figure P).

Figure P

Step 13: Remove the plunger from the oral syringe barrel by pulling the plunger and barrel away from each other. Rinse the oral syringe (plunger and barrel) with water only (see Figure Q). Allow it to air dry.

Figure Q

Step 14: When the oral syringe (plunger and barrel) are dry, put the plunger back into the oral syringe barrel. Do not throw away the oral syringe. Store the oral syringe in a clean, dry place.

Marketed and distributed by:

Tanabe Pharma America, Inc.

Jersey City, NJ 07310

For more information, go to www.Radicava.com or call 1- 888-292-0058.

RADICAVA ORS® is a registered trademarks of K.K. BCJ-94.

© 2025 Tanabe Pharma America, Inc. All rights reserved.

This Instructions for Use has been approved by the U.S. Food and Drug Administration. 22022-3

Issued: 12/2025